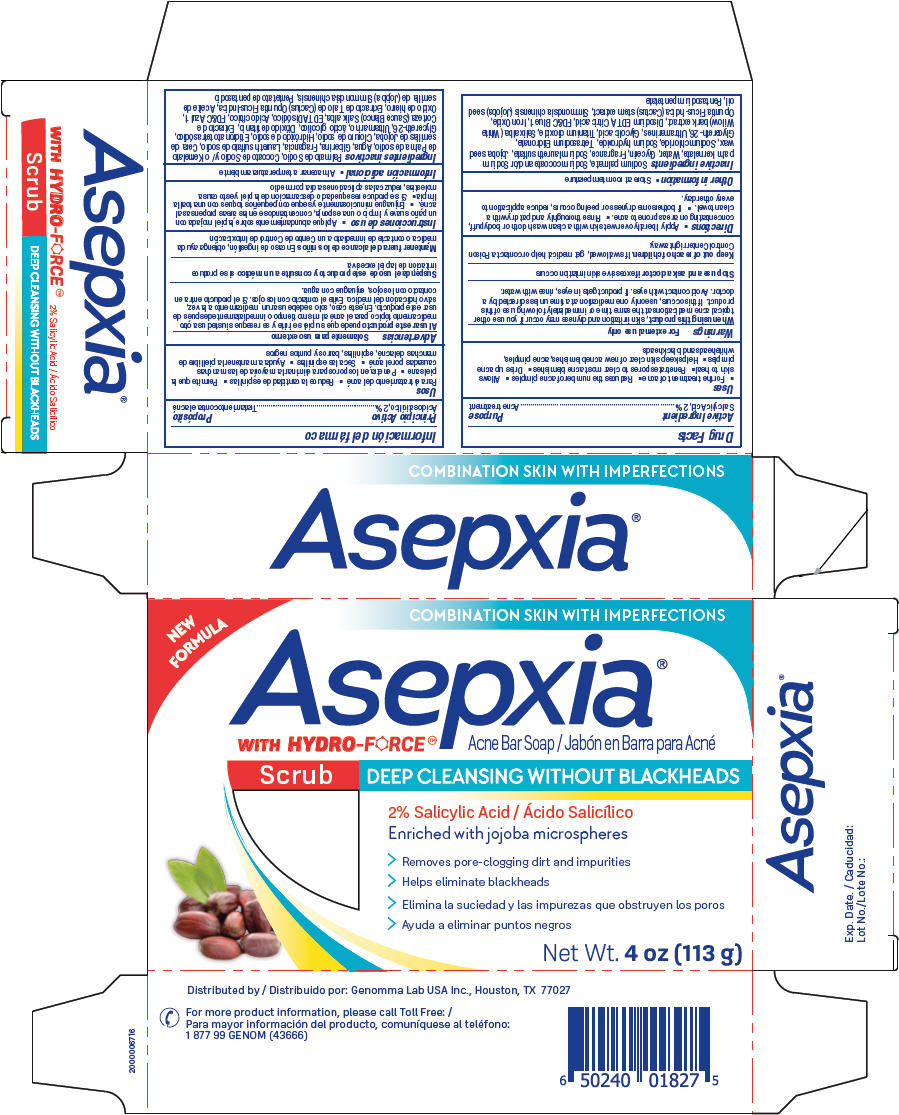 DRUG LABEL: Asepxia Scrub Acne Bar
NDC: 50066-804 | Form: SOAP
Manufacturer: Genomma Lab USA
Category: otc | Type: HUMAN OTC DRUG LABEL
Date: 20231106

ACTIVE INGREDIENTS: SALICYLIC ACID 2 g/100 g
INACTIVE INGREDIENTS: SODIUM PALMATE; SODIUM COCOATE; SODIUM PALM KERNELATE; WATER; GLYCERIN; SODIUM LAURETH-3 SULFATE; SIMMONDSIA CHINENSIS SEED WAX; SODIUM CHLORIDE; SODIUM HYDROXIDE; ETIDRONATE TETRASODIUM; GLYCERETH-26; ULTRAMARINE BLUE; GLYCOLIC ACID; TITANIUM DIOXIDE; EDETATE DISODIUM ANHYDROUS; CITRIC ACID MONOHYDRATE; FD&C BLUE NO. 1; FERRIC OXIDE RED; OPUNTIA FICUS-INDICA STEM; JOJOBA OIL; PENTASODIUM PENTETATE

Asepxia Scrub Acne Bar Soap®

Active Ingredient

Salicylic Acid, 2%

Purpose

Acne treatment

Uses

- For the treatment of acne
- Reduces the number of acne pimples
- Allows skin to heal
- Penetrates pores to clear most acne blemishes
- Dries up acne pimples
- Helps keep skin clear of new acne blemishes, acne pimples, whiteheads and blackheads

Warnings

For external use only

WHEN USING

, skin irritation and dryness may occur if you use other topical acne medications at the same time or immediately following use of this product. If this occurs, use only one medication at a time unless directed by a doctor. Avoid contact with eyes. If product gets in eyes, rinse with water. When using this product

STOP USE

excessive skin irritation occurs Stop use and ask a doctor if

KEEP OUT OF REACH OF CHILDREN

. If swallowed, get medical help or contact a Poison Control Center right away. Keep out of reach of children

Directions

- Apply liberally over wet skin with a clean wash cloth or body puff, concentrating on areas prone to acne.
- Rinse thoroughly and pat dry with a clean towel.
- If bothersome dryness or peeling occurs, reduce application to every other day.

Other information

- Store at room temperature

Inactive ingredients

Sodium palmate, Sodium cocoate and/or Sodium palm kernelate, Water, Glycerin, Fragrance, Sodium laureth sulfate, Jojoba seed wax, Sodium chloride, Sodium hydroxide, Tetrasodium Etidronate, Glycereth-26, Ultramarines, Glycolic acid, Titanium dioxide, Salix alba (White Willow) bark extract, Disodium EDTA, Citric acid, FD&C Blue 1, Iron Oxide, Opuntia Ficus-Indica (Cactus) stem extract, Simmondsia chinensis (Jojoba) seed oil, Pentasodium pentetate

QUESTIONS

For more product information, please call Toll Free: 1 877 99 GENOM (43666)

Distributed by: Genomma Lab USA Inc., Houston, TX 77027

PRINCIPAL DISPLAY PANEL - 113 g Bar Carton

NEW FORMULA

COMBINATION SKIN WITH IMPERFECTIONS

Asepxia WITH HYDRO-FORCE™®

Acne Bar Soap

Scrub DEEP CLEANSING WITHOUT BLACKHEADS

2% Salicylic Acid Enriched with jojoba microspheres

> Removes pore-clogging dirt and impurities

> Helps eliminate blackheads

Net Wt. 4 oz (113 g)